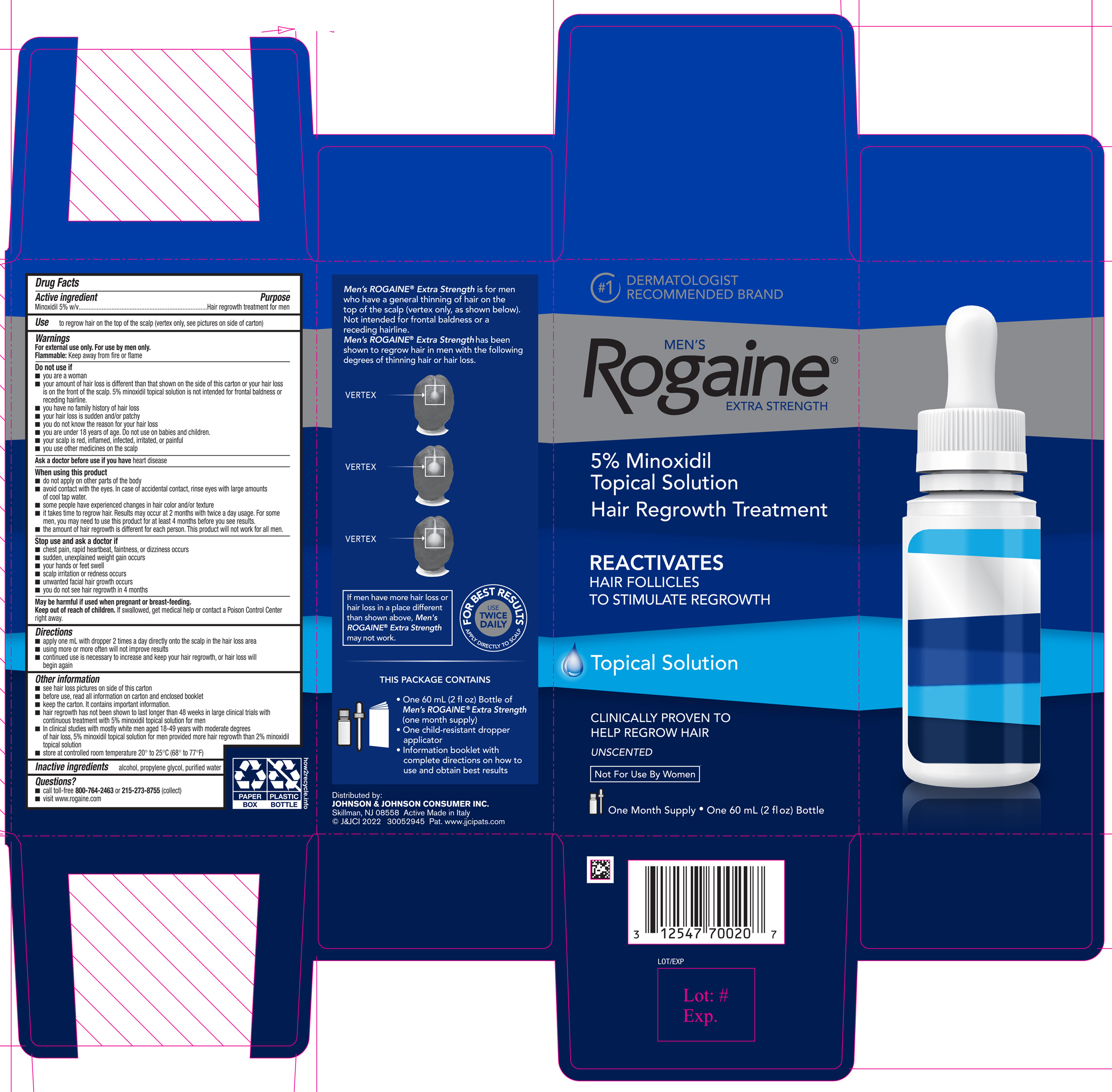 DRUG LABEL: Mens Rogaine Extra Strength Unscented
NDC: 69968-0089 | Form: SOLUTION
Manufacturer: Kenvue Brands LLC
Category: otc | Type: HUMAN OTC DRUG LABEL
Date: 20240906

ACTIVE INGREDIENTS: MINOXIDIL 50 mg/1 mL
INACTIVE INGREDIENTS: ALCOHOL; PROPYLENE GLYCOL; WATER

MEN'S Rogaine® EXTRA STRENGTH UNSCENTED

Drug Facts

Active ingredient

Minoxidil 5% w/v

Purpose

Hair regrowth treatment for men

Use

to regrow hair on the top of the scalp (vertex only, see pictures on side of carton)

Warnings

For external use only. For use by men only.

Flammable: Keep away from fire or flame

Do not use if

- you are a woman
- your amount of hair loss is different than that shown on the side of this carton or your hair loss is on the front of the scalp. 5% minoxidil topical solution is not intended for frontal baldness or receding hairline.
- you have no family history of hair loss
- your hair loss is sudden and/or patchy
- you do not know the reason for your hair loss
- you are under 18 years of age. Do not use on babies and children.
- your scalp is red, inflamed, infected, irritated, or painful
- you use other medicines on the scalp

Ask a doctor before use if you have heart disease

When using this product

- do not apply on other parts of the body
- avoid contact with the eyes. In case of accidental contact, rinse eyes with large amounts of cool tap water.
- some people have experienced changes in hair color and/or texture
- it takes time to regrow hair. Results may occur at 2 months with twice a day usage. For some men, you may need to use this product for at least 4 months before you see results.
- the amount of hair regrowth is different for each person. This product will not work for all men.

Stop use and ask a doctor if

- chest pain, rapid heartbeat, faintness, or dizziness occurs
- sudden, unexplained weight gain occurs
- your hands or feet swell
- scalp irritation or redness occurs
- unwanted facial hair growth occurs
- you do not see hair regrowth in 4 months

PREGNANCY OR BREAST FEEDING

May be harmful if used when pregnant or breast-feeding.

Keep out of reach of children. If swallowed, get medical help or contact a Poison Control Center right away.

Directions

- apply one mL with dropper 2 times a day directly onto the scalp in the hair loss area
- using more or more often will not improve results
- continued use is necessary to increase and keep your hair regrowth, or hair loss will begin again

Other information

- see hair loss pictures on side of this carton
- before use, read all information on carton and enclosed booklet
- keep the carton. It contains important information.
- hair regrowth has not been shown to last longer than 48 weeks in large clinical trials with continuous treatment with 5% minoxidil topical solution for men
- In clinical studies with mostly white men aged 18-49 years with moderate degrees of hair loss, 5% minoxidil topical solution for men provided more hair regrowth than 2% minoxidil topical solution
- store at controlled room temperature 20º to 25º C (68º to 77º F)

Inactive ingredients

alcohol, propylene glycol, purified water

Questions?

- call toll-free 800-764-2463 or 215-273-8755 (collect)
- visit www.rogaine.com

Distributed by:
JOHNSON & JOHNSON CONSUMER INC.
Skillman,NJ 08558

PRINCIPAL DISPLAY PANEL - 60 mL Bottle Carton

#1 DERMATOLOGIST
RECOMMENDED BRAND
MEN'S

Rogaine®
EXTRA STRENGTH

5% Minoxidil
Topical Solution
Hair Regrowth Treatment
REACTIVATES
HAIR FOLLICLES
TO STIMULATE REGROWTH
Topical Solution

CLINICALLY PROVEN TO
HELP REGROW HAIR
UNSCENTED

Not For Use By Women

One Month Supply. One 60 mL (2 fl oz) Bottle